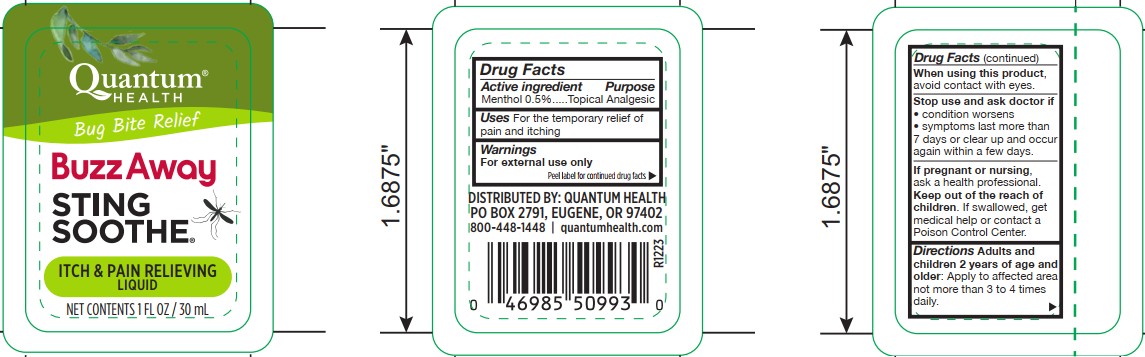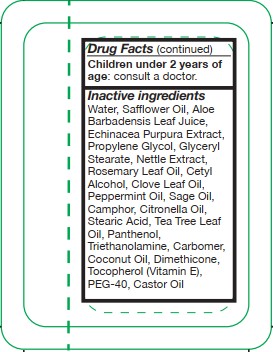 DRUG LABEL: Buzz Away Sting Soothe
NDC: 70084-810 | Form: LIQUID
Manufacturer: Quantum, Inc.
Category: otc | Type: HUMAN OTC DRUG LABEL
Date: 20251020

ACTIVE INGREDIENTS: MENTHOL 5 mg/1 mL
INACTIVE INGREDIENTS: URTICA DIOICA LEAF; SAFFLOWER OIL; ECHINACEA PURPUREA; SAGE OIL; CAMPHOR (NATURAL); CARBOMER; WATER; CLOVE LEAF OIL; COCONUT OIL; STEARIC ACID; TRIETHANOLAMINE; TOCOPHEROL; PEPPERMINT OIL; CITRONELLA OIL; TEA TREE OIL; PANTHENOL; DIMETHICONE; ALOE BARBADENSIS LEAF JUICE; PROPYLENE GLYCOL; CETYL ALCOHOL; PEG-40; CASTOR OIL; GLYCERYL STEARATE; ROSEMARY OIL

Buzz Away Sting Soothe

Active ingredient

Menthol 0.5%

Purpose

Menthol 0.5%...............Topical Analgesic

Uses

For the temporary relief ofpain and itching

Warnings

For external use only

When using this product, avoiid contact with eyes.

Stop use and ask doctor if

• condition worsens

• symptoms last more than7 days or clear up and occuragain within a few days.

PREGNANCY OR BREAST FEEDING

If pregnant or nursing, ask a health professional.

KEEP OUT OF REACH OF CHILDREN

Keep out of the reach of children. If swallowed, get medical help or contact a Poison Control Center.

Directions

Adults and children 2 years of age and older: Apply to affected area not more than 3 to 4 times daily

Children under 2 years of age: consult a doctor.

Inactive ingredients

Water, Safflower Oil, Aloe Barbadensis Leaf Juice, Echinacea Purpura Extract, Propylene Glycol, Glyceryl Stearate, Nettle Extract, Rosemary Leaf Oil, Cetyl Alcohol, Clove Leaf Oil, Peppermint Oil, Sage Oil, Camphor, Citronella Oil, Stearic Acid, Tea Tree Leaf Oil, Panthenol, Triethanolamine, Carbomer, Coconut Oil, Dimethicone, Tocopherol (Vitamin E), PEG-40, Castor Oil

PACKAGE LABEL

Quantum Health

Bug Bite Relief

Buzz Away

Sting Soothe

Itch & Pin Relieving Liquid

Net Contents 1 Fl Oz / 30 mL